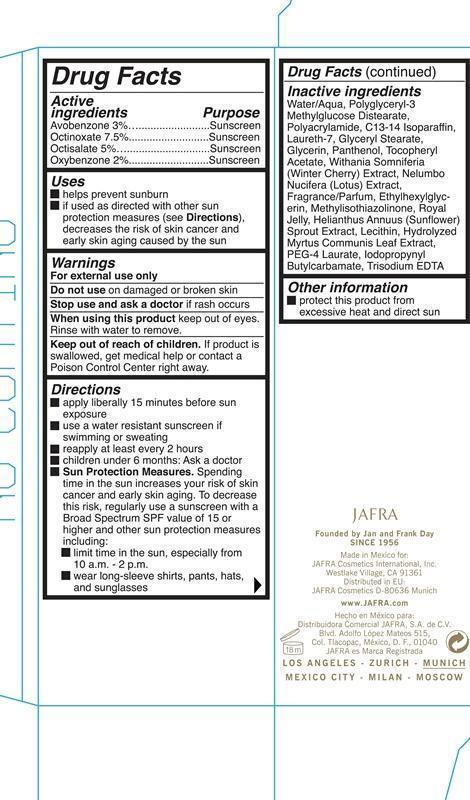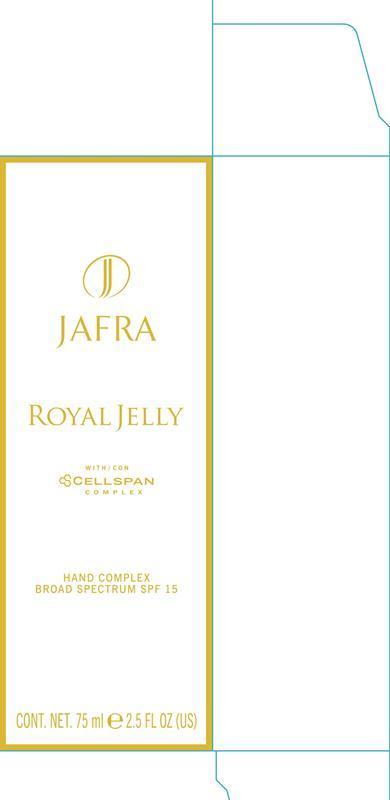 DRUG LABEL: Hand Complex Broad Spectrum SPF 15
NDC: 68828-124 | Form: JELLY
Manufacturer: JAFRA COSMETICS INTERNATIONAL
Category: otc | Type: HUMAN OTC DRUG LABEL
Date: 20190415

ACTIVE INGREDIENTS: AVOBENZONE 3 g/75 mL; OCTINOXATE 7.5 g/75 mL; OCTISALATE 5 g/75 mL; OXYBENZONE 2 g/75 mL
INACTIVE INGREDIENTS: WATER; POLYACRYLAMIDE (10000 MW); C13-14 ISOPARAFFIN; LAURETH-7; GLYCERYL MONOSTEARATE; GLYCERIN; PANTHENOL; .ALPHA.-TOCOPHEROL ACETATE; ETHYLHEXYLGLYCERIN; METHYLISOTHIAZOLINONE; ROYAL JELLY; HELIANTHUS ANNUUS SPROUT; EGG PHOSPHOLIPIDS; PEG-4 LAURATE; IODOPROPYNYL BUTYLCARBAMATE; EDETATE TRISODIUM

Hand Complex Broad Spectrum SPF 15

Active Ingredients Purpose

Avobenzone 3% Sunscreen

Octinoxate 7.5% Sunscreen

Octisalate 5% Sunscreen

Oxybenzone 2% Sunscreen

Uses

helps prevent sunburn

if used as directed with other sun protection measures (see Directions), decreases the risk of skin cancer and early skin aging caused by the sun.

Keep out of reach of children. If product is swallowed, get medical help or contact a Poison Control Cneter right away.

Stop use and ask a doctor if rash occurs

Warnings

For external use only

Do not use on damaged or broken skin

when using this product, keep out of eyes. Rinse with water to remove.

Directions

apply liberally 15 minutes before sun exposure

use a water resistant sunscreen if swimming or sweating

reapply at least every 2 hours

children under 6 months: Ask a doctor

Sun Protection Measures.

Spending time in the sun increases your risk of skin cancer and early skin aging. To decrease this risk, regularly use a sunscreen with a Broad Spectrum SPF value of 15 or higher and other sunscreen measures including:

limit time in the sun, especially from 10a.m.- 2 p.m.

wear long-sleeve shirts, pants, hats, and sunglasses

Inactive

Water/Aqua, Polyglyceryl-3 Methylglucose Distearate, Polyacrylamide, C13-14 Isoparaffin, Laureth-7, Glyceryl Stearate, Glycerin, Panthenol, Tocopheryl Acetate, Withania Somnifera (Winter Cherry) Extract, Nelumbo Nucifera (Lotus) Extract, Fragrance/Parfum, Ethylhexyglycerin, Methylisothiazolinone, Royal Jelly, Helianthus Annuus (Sunflower) Sprout Extract, Lecithin, Hydrolyzed Myrtus Communis Leaf Extract, PEG-4 Laurate, Iodopropynyl Butylcarbamate, Trisodium EDTA

PACKAGE LABEL

Jafra

Royal Jelly

with/con

Cellspan Complex

Hand Complex Broad Spectrum SPF 15

Cont. Net. 75 ml 2.5 fl oz (US)